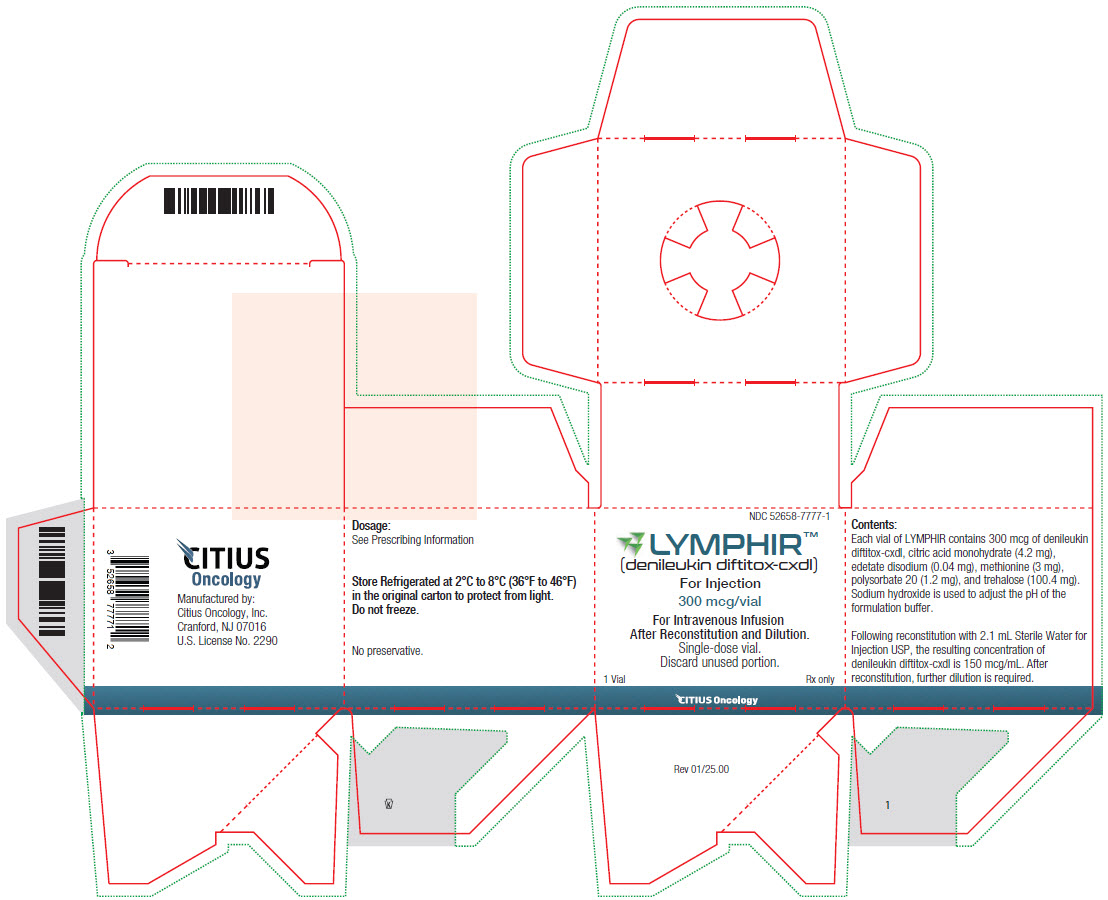 DRUG LABEL: LYMPHIR
NDC: 52658-7777 | Form: INJECTION, POWDER, LYOPHILIZED, FOR SOLUTION
Manufacturer: Citius Pharmaceuticals, Inc.
Category: prescription | Type: HUMAN PRESCRIPTION DRUG LABEL
Date: 20250123

ACTIVE INGREDIENTS: DENILEUKIN DIFTITOX 300 ug/2 mL
INACTIVE INGREDIENTS: CITRIC ACID MONOHYDRATE 4.2 mg/2 mL; EDETATE DISODIUM 0.04 mg/2 mL; METHIONINE 3 mg/2 mL; POLYSORBATE 20 1.2 mg/2 mL; TREHALOSE DIHYDRATE 100.4 mg/2 mL; SODIUM HYDROXIDE

HIGHLIGHTS OF PRESCRIBING INFORMATION

These highlights do not include all the information needed to use LYMPHIR™ safely and effectively. See full prescribing information for LYMPHIR.
LYMPHIR™ (denileukin diftitox-cxdl) for injection, for intravenous use
Initial U.S. Approval: 2024

WARNING: CAPILLARY LEAK SYNDROME

See full prescribing information for complete boxed warning.

- Capillary leak syndrome (CLS), including life-threatening or fatal reactions, can occur in patients receiving LYMPHIR. Monitor patients for signs and symptoms of CLS during treatment. Withhold LYMPHIR until CLS resolves or permanently discontinue based on severity. (2.1, 2.4, 5.1)

1 INDICATIONS AND USAGE

LYMPHIR is an IL2-receptor-directed cytotoxin indicated for the treatment of adult patients with relapsed or refractory Stage I-III cutaneous T-cell lymphoma (CTCL) after at least one prior systemic therapy. (1)

2 DOSAGE AND ADMINISTRATION

- Delay start of treatment cycle if serum albumin level is below 3 g/dL. (2.1)
- The recommended dosage of LYMPHIR is 9 mcg/kg/day actual body weight administered as an intravenous infusion on Days 1 through 5 of a 21-day cycle. (2.2)
- Administer premedication as recommended. (2.3)
- See full prescribing information for preparation and administration instructions. (2.5)

3 DOSAGE FORMS AND STRENGTHS

For injection: 300 mcg lyophilized cake in a single-dose vial.

4 CONTRAINDICATIONS

None. (4)

5 WARNINGS ANDPRECAUTIONS

- Visual Impairment: Monitor and evaluate for visual impairment throughout treatment. Withhold LYMPHIR until visual impairment resolves or permanently discontinue based on severity. (5.2)
- Infusion-Related Reactions: Monitor patients closely during infusions. Interrupt or discontinue for infusion-related reactions based on severity. (5.3)
- Hepatotoxicity: Monitor liver enzymes and bilirubin at baseline and during treatment as clinically indicated. (5.4)
- Embryo-Fetal Toxicity: Can cause fetal harm. Advise females of reproductive potential of the potential risk to a fetus and to use effective contraception. (5.5, 8.1, 8.3)

6 ADVERSE REACTIONS

The most common adverse reactions (≥20%), including laboratory abnormalities, are increased transaminases, albumin decreased, nausea, edema, hemoglobin decreased, fatigue, musculoskeletal pain, rash, chills, constipation, pyrexia, and capillary leak syndrome. (6.1)

To report SUSPECTED ADVERSE REACTIONS, contact Citius Oncology, Inc. at 1-844-459-6744 or FDA at 1-800-FDA-1088 or www.fda.gov/medwatch.

8 USE IN SPECIFIC POPULATIONS

Lactation:Advise not to breastfeed. (8.2)

FULL PRESCRIBING INFORMATION

WARNING: CAPILLARY LEAK SYNDROME

Capillary leak syndrome (CLS), including life-threatening or fatal reactions, can occur in patients receiving LYMPHIR. Monitor patients for signs and symptoms of CLS during treatment. Withhold LYMPHIR until CLS resolves, or permanently discontinue based on severity [see Dosage and Administration (2.1, 2.4) and Warnings and Precautions (5.1)] .

1 INDICATIONS AND USAGE

LYMPHIR is indicated for the treatment of adult patients with relapsed or refractory Stage I-III cutaneous T-cell lymphoma (CTCL) after at least one prior systemic therapy.

2 DOSAGE AND ADMINISTRATION

2.1 Important Dosing Instructions

Prior to starting each treatment cycle, assess hepatic and renal function. If serum albumin is less than 3 g/dL, delay administration of LYMPHIR until serum albumin is greater than or equal to 3 g/dL [see Warnings and Precautions (5.1)] .

2.2 Recommended Dosage

The recommended dosage of LYMPHIR is 9 mcg/kg/day actual body weight administered as an intravenous infusion over 60 minutes on Days 1 through 5 of a 21-day treatment cycle. Administer LYMPHIR until disease progression or unacceptable toxicity.

2.3 Recommended Premedications

Administer premedications prior to starting a LYMPHIR infusion in Cycles 1 through 3, as outlined in Table 1, to reduce the risk of infusion-related reactions [see Warnings and Precautions (5.3)] .

Table 1. Premedication to be Administered to Patients Prior to LYMPHIR Infusion
Treatment Cycle | Premedication | Dosage | Administration
Cycles 1-3 (optional thereafter) | Antipyretic | Oral acetaminophen 650 mg or per local institutional guidelines | At least 30 minutes prior to infusion
Cycles 1-3 (optional thereafter) | Antihistamine | Diphenhydramine 25 mg intravenously or other antihistamine per local institutional guidelines | At least 30 minutes prior to infusion
Cycles 1-3 (optional thereafter) | Antiemetic | Per institutional guidelines | At least 30 minutes prior to infusion
 | Hydration | 250 to 500 mL 0.9% Sodium Chloride Injection intravenously (or other amount of fluid considered to be most appropriate for the; subject’s condition) | At least 30 minutes prior to infusion

If patients experience a Grade 2 or higher infusion reaction, premedicate at least 30 minutes prior to each subsequent infusion with a systemic steroid such as dexamethasone 4 mg (or equivalent) via slow intravenous push, for at least 3 cycles.

2.4 Dosage Modifications for Adverse Reactions

Dosage modifications for adverse reactions with LYMPHIR are shown in Table 2 below.

Table 2: Recommended Dosage Modifications for Adverse Reactions
Adverse Reaction | Severity* | Dosage Modification
Capillary leak syndrome (CLS) [see Warnings and Precautions (5.1)] | Grade 2 | - Withhold LYMPHIR until CLS resolves to Grade 1.
Capillary leak syndrome (CLS) [see Warnings and Precautions (5.1)] | Grade 3 | - Withhold LYMPHIR and provide supportive care until CLS resolves to Grade 1. - Resume LYMPHIR at 50% dose. - Consider steroid premedication for subsequent infusions. - Permanently discontinue upon recurrence.
 | Grade 4 | - Permanently discontinue LYMPHIR.
Visual impairment [see Warnings and Precautions (5.2)] | Grade 1 or 2 | - Consider withholding or discontinuing LYMPHIR as appropriate. - Refer for ophthalmic evaluation.
 | Grade 3 or 4 | - Withhold LYMPHIR until resolved to Grade 1 or baseline. - Refer for ophthalmic evaluation. - Permanently discontinue LYMPHIR if impairment does not resolve to Grade 1 or baseline.
Infusion-related reactions [see Warnings and Precautions (5.3)] | Grade 2 or 3 | - Interrupt infusion and manage signs and symptoms. - Administer steroid premedication prior to the subsequent doses of LYMPHIR [see Dosage and Administration (2.3)] - Continue steroid premedication for each dose in the next 3 cycles and optional thereafter [see Dosage and Administration (2.3)]
 | Grade 4 or; Recurrent; Grade 3 | - Permanently discontinue LYMPHIR.
Hepatotoxicity [see Warnings and Precautions (5.4)] | Grade 2: ALT/AST 3 to 5 x upper limit of normal (ULN) | - Maintain LYMPHIR dose - Monitor at least weekly until return to < 3 x ULN
 | Grade 3: ALT/AST > 5 to 20 x ULN | - Withhold LYMPHIR and monitor at least weekly until return to < 3 x ULN - Resume LYMPHIR at same dose (first occurrence) or at a reduced dose (50%) for subsequent occurrence
 | Grade 4: ALT/AST > 20 x ULN | - Permanently discontinue LYMPHIR
Other Adverse Reactions [see Adverse Reactions (6.1)] | Grade 3 | - Withhold LYMPHIR until resolution of toxicity to Grade 1 or baseline.
 | Grade 4 | - Permanently discontinue LYMPHIR as appropriate.

* Based on NCI CTCAE version 5.0

Restarting after Dosage Delay Due to Toxicity

Time Since the Last Dose Administered | Action for Next Dose
Less than or equal to 16 days | Restart a new cycle no earlier than 16 days after last dose of LYMPHIR
More than 16 days | Restart a new cycle of LYMPHIR
More than 42 days | Permanently discontinue LYMPHIR

2.5 Preparation and Administration

Reconstitute and further dilute LYMPHIR prior to administration. Administer as an intravenous infusion over 60 minutes. Use aseptic technique to prepare LYMPHIR.

LYMPHIR does not contain a preservative or anti-microbial agent. Care should be taken during preparation and administration of LYMPHIR to prevent inadvertent microbial contamination.

Reconstitution

- Calculate the dose (mcg), total volume (mL) of solution required, and number of vials of LYMPHIR needed based on the patient’s actual body weight (kg). More than one vial may be needed for a full dose.
- Remove the vial(s) of LYMPHIR from the refrigerator and allow to stand for approximately 30 minutes to reach to room temperature [20°C to 25°C (68°F to 77°F)].
- Reconstitute each LYMPHIR vial with 2.1 mL of Sterile Water for Injection to obtain a final concentration of 150 mcg/mL. If more than one vial is needed to make a complete dose, use a separate syringe and needle for each vial.
- Gently swirl the vial. Do not shake.
- Parenteral drug products should be inspected visually for particulate matter and discoloration prior to administration, whenever solution and container permit. The reconstituted solution should be clear and colorless. Discard if the solution is not clear, colorless, and contains particulate matter.
- Use the reconstituted LYMPHIR solution immediately to prepare the drug product.

Dilution

- Use only plastic syringes or soft plastic intravenous bags. Do notuse glass containers.
- Maintain concentration of LYMPHIR at 15 mcg/mL or higher during all steps in the preparation of the solution for intravenous infusion.
- Withdraw the calculated dose from the vial(s) with a sterile syringe and inject it into an empty intravenous bag.
- Dilute with 0.9% Sodium Chloride Injection to final concentration of 15 mcg/mL or higher.
- Parenteral drug products should be inspected visually for particulate matter and discoloration prior to administration, whenever solution and container permit. Do not use if the prepared solution is cloudy or particulates are present.
- If not used immediately, store the diluted LYMPHIR solution at room temperature [20°C to 25°C (68°F to 77°F)] for up to 4 hours. Protect diluted solution from light.

Administration

- Administer infusion solution intravenously over 60 minutes through an intravenous line using a syringe pump or intravenous infusion bag. Do not administer through in-line filter.
- Do not mix LYMPHIR with other drugs or administer other drugs through the same infusion line.
- At the end of the infusion, discard any empty or unused portions of LYMPHIR immediately.

3 DOSAGE FORMS AND STRENGTHS

For injection: 300 mcg/vial, sterile, white lyophilized cake in a single-dose vial for reconstitution and further dilution.

4 CONTRAINDICATIONS

None.

5 WARNINGS ANDPRECAUTIONS

5.1 Capillary Leak Syndrome

LYMPHIR can cause capillary leak syndrome (CLS), including life-threatening or fatal reactions. CLS was defined in the clinical trials as the occurrence of at least 2 of the following symptoms at any time during LYMPHIR therapy: hypotension, edema, and serum albumin <3 g/dL. These symptoms were not required to occur simultaneously to be characterized as capillary leak syndrome.

As defined, CLS occurred in 27% of patients in the pooled population across 3 clinical trials, including 8% with Grade 3. There was one (0.8%) fatal occurrence of CLS. Of the patients with CLS, 22% had recurrence. The majority of CLS events (81%) occurred within the first 2 cycles of treatment. The median time to onset from Cycle 1, Day 1 was 6.5 days (range: 1 to 77), the median duration of CLS was 14 days (range: 2 to 40), and 75% of patients had resolution. The most common symptoms included edema, hypoalbuminemia, and hypotension. Pleural effusion, pericardial effusion, and dehydration also occurred.

Regularly assess patients for weight gain, new onset or worsening of edema, dyspnea, and hypotension (including orthostatic changes). Monitor serum albumin levels prior to the initiation of each cycle of therapy and more often as clinically indicated.

Withhold, reduce dose, or permanently discontinue based on severity. If LYMPHIR is withheld, resume LYMPHIR following resolution of CLS and when serum albumin is greater than or equal to 3 g/dL [see Dosage and Administration (2.1and 2.4)] .

5.2 Visual Impairment

LYMPHIR can cause serious visual impairment, including changes in visual acuity and color vision. In the pooled population across 3 clinical trials, visual impairment occurred in 9%, with Grade 1 in 8% and Grade 2 in 1%. The most commonly reported symptom was blurred vision. Of the patients with visual impairment, 67% had resolution of their visual impairment.

Perform baseline ophthalmic examination and monitor as clinically indicated. If patients experience symptoms of visual impairment, such as changes in visual acuity, changes in color vision, or blurred vision, refer for ophthalmologic evaluation.

Withhold LYMPHIR until visual impairment resolves or permanently discontinue based on severity [see Dosage and Administration (2.4)] .

5.3 Infusion-Related Reactions

LYMPHIR can cause serious infusion-related reactions. Infusion-related reactions were reported in 69% of patients in the pooled population across 3 clinical trials of patients who received LYMPHIR, with Grade 3 infusion-related reactions in 3.4% [see Adverse Reactions (6.1)] . Eighty-three percent of infusion-related reactions occurred in Cycles 1 and 2. The most common symptoms included nausea, fatigue, chills, musculoskeletal pain, vomiting, fever, and arthralgia.

Premedicate patients for the first three cycles prior to starting a LYMPHIR infusion [see Dosage and Administration (2.3)] . Monitor patients frequently during infusion. For Grade 2 or higher infusion reactions, premedicate at least 30 minutes prior to each subsequent infusion with a systemic steroid for at least 3 cycles [see Dosage and Administration (2.3)] .

Interrupt or discontinue LYMPHIR based on severity [see Dosage and Administration (2.4)]. Institute appropriate medical management.

5.4 Hepatotoxicity

LYMPHIR can cause hepatotoxicity. In the pooled safety population, elevated ALT occurred in 70% of patients, with Grade 3 ALT occurring in 22%; elevated AST occurred in 64% of patients, with Grade 3 AST elevation occurring in 9%. For Grade 3 events, median time to onset was 8 days (range: 1 to 15 days); median time to resolution was 15 days (range: 7 to 50 days); all cases of Grade 3 ALT or AST elevations resolved [see Adverse Reactions (6.1)]. Elevated total bilirubin occurred in 5% of patients, with Grade 3 occurring in 0.9%.

Monitor liver enzymes and bilirubin at baseline and during treatment as clinically indicated. Withhold, reduce dose, or permanently discontinue LYMPHIR based on severity [see Dosage and Administration (2.4)] .

5.5 Embryo-Fetal Toxicity

Based on its mechanism of action, LYMPHIR can cause fetal harm when administered to a pregnant woman. Verify the pregnancy status of females of reproductive potential prior to the initiation of LYMPHIR. Advise pregnant women of the potential risk to the fetus. Advise females of reproductive potential to use effective contraception during treatment and for 7 days following the last dose of LYMPHIR [see Use in Specific Populations (8.1, 8.3)] .

6 ADVERSE REACTIONS

The following adverse reactions are discussed in greater detail in other sections of the label:

- Capillary Leak Syndrome [see Warnings and Precautions (5.1)]
- Visual Impairment [see Warnings and Precautions (5.2)]
- Infusion-Related Reactions [see Warnings and Precautions (5.3)]
- Hepatotoxicity [see Warnings and Precautions (5.4)]

6.1 Clinical Trials Experience

Because clinical trials are conducted under widely varying conditions, adverse reaction rates observed in the clinical trials of a drug cannot be directly compared to rates in the clinical trials of another drug and may not reflect the rates observed in practice.

The pooled safety population described in the WARNINGS AND PRECAUTIONS reflect exposure to LYMPHIR as a single agent in 119 patients with CTCL across 3 clinical trials. Patients received treatment with LYMPHIR as an intravenous infusion at 9 mcg/kg daily from Day 1 through Day 5 of each 21-day cycle until disease progression or unacceptable toxicity. Among 119 patients who received LYMPHIR the median number of cycles received was 5 (range: 1 to 42), with 13% exposed for 6 months or longer.

In this pooled safety population, the most common (≥ 20%) adverse reactions, including laboratory abnormalities, were increased transaminases (70%), albumin decreased (53%), nausea (40%), edema (35%), hemoglobin decreased (34%), fatigue (30%), musculoskeletal pain (26%), rash (23%), chills (22%), constipation (22%), pyrexia (21%), and capillary leak syndrome (20%).

Relapsed or Refractory Stage I-III CTCL

Study 302

The safety of LYMPHIR was evaluated in Study 302, an open-label, single-arm, multicenter trial that included 69 patients with relapsed or refractory Stage I-III CTCL [see Clinical Studies (14)] . Patients received treatment with LYMPHIR 9 mcg/kg daily from Day 1 through Day 5 of each 21-day cycle. Treatment was administered until disease progression or unacceptable toxicity. The median number of LYMPHIR cycles was 6 (range: 1 to 42).

The median age of patients was 64 years (range: 28 to 87 years), 49% were 65 years of age or older, 65% were men, 72% were White, 19% were Black or African American, 1.4% were Asian, and 14% were Hispanic or Latino.

Serious adverse reactions occurred in 38% of patients who received LYMPHIR. Serious adverse reactions in > 2% of patients included capillary leak syndrome (10%), infusion-related reaction (9%), sepsis (7%), skin infection (2.9%), pyrexia (2.9%), and rash (2.9%).

Permanent discontinuation of LYMPHIR due to an adverse reaction occurred in 12% of patients. Adverse reactions resulting in permanent discontinuation of LYMPHIR included capillary leak syndrome, infusion-related reaction, renal insufficiency, respiratory failure, and sepsis.

Dosage interruptions of LYMPHIR due to an adverse reaction occurred in 38% of patients. Adverse reactions requiring dosage interruption of LYMPHIR included capillary leak syndrome, infusion-related reaction, weight increase, nausea, and tachycardia.

Table 3 summarizes the adverse reactions in Study 302.

Table 3: Adverse Reactions (≥ 10%) in Patients with Relapsed or Refractory Stage I-III CTCL Who Received LYMPHIR in Study 302
Adverse Reaction | LYMPHIR; N=69
 | All Grades; (%) | Grade 3 or 4; (%)
Gastrointestinal disorders
Nausea | 43 | 1.4#
Diarrhea | 19 | 0
Vomiting | 13 | 0
Constipation | 12 | 0
General disorders and administration site conditions
Fatiguea | 38 | 0
Edemab | 33 | 1.4
Chills | 27 | 1.4
Pyrexia | 16 | 1.4
Musculoskeletal and connective tissue disorders
Musculoskeletal painc | 27 | 2.9
Arthralgia | 12 | 0
Nervous system disorders
Headached | 25 | 0
Dizziness | 13 | 0
Mental status changese | 13 | 0
Injury, poisoning and procedural complications
Infusion-related reaction | 25 | 6
Skin and subcutaneous tissue disorders
Rashf | 23 | 6
Pruritis | 19 | 6
Vascular disorders
Capillary leak syndrome | 17 | 6
Metabolism and nutrition disorders
Decreased appetite | 13 | 1.4
Eye disorders
Blurred vision | 13 | 0
Investigations
Weight increased | 13 | 0
Infections and infestations
Skin infectiong | 13 | 1.4
Renal and urinary disorders
Renal insufficiencyh | 12 | 2.9
Psychiatric disorders
Insomnia | 10 | 0

#Only Grade 3 adverse reaction occurred
aIncludes fatigue, asthenia, and lethargy
bIncludes edema, edema peripheral, generalized edema, face edema, swelling face, peripheral swelling
cIncludes musculoskeletal pain, back pain, neck pain, pain in extremity, myalgia, bone pain
dIncludes headache, migraine
eIncludes amnesia, confusional state, delirium, memory impairment, disturbance in attention, somnolence, cognitive disorder
fIncludes rash, drug eruption, erythema, rash maculo-papular, rash papular, rash pustular, rash pruritic, dermatitis exfoliative generalized, acute generalized exanthematous pustulosis
gIncludes skin infection, skin bacterial infection, staphylococcal skin infection, impetigo
hIncludes acute kidney injury, blood creatinine increased

Clinically relevant adverse reactions in < 10% of patients who received LYMPHIR included sepsis and peripheral neuropathy.

Table 4 summarizes select laboratory abnormalities in Study 302.

Table 4: Select Laboratory Abnormalities (≥ 10%) that Worsened from Baseline in Patients with Relapsed or Refractory Stage I-III CTCL who Received LYMPHIR in Study 302
Laboratory Abnormalitya,b | Any Gradec (%)b | Grade 3 or 4c (%)
Chemistry
Alanine aminotransferase increased | 66 | 13
Aspartate aminotransferase increased | 60 | 4.5
Albumin decreased | 43 | 1.5
Creatine phosphokinase increasedd | 22 | 3
Alkaline phosphatase increased | 18 | 0
Hematology
Lymphocyte count decreased | 52 | 20
Hemoglobin decreased | 34 | 1.5

aGraded according to NCI CTCAE version 5.0
bThe denominator used to calculate the rate was 67 based on the number of patients with a baseline value and at least one post-treatment value
cPercentage of patients with an increase of at least 1 CTCAE grade from baseline to the worst post-baseline value of any grade, or to the worst post-baseline value that is Grade 3 or 4
dThe denominator used to calculate the rate was based on 36 patients with a baseline value and at least one post-treatment value.

6.2 Postmarketing Experience

The following adverse reactions have been identified during post-approval use of denileukin diftitox. Because these reactions are reported voluntarily from a population of uncertain size, it is not always possible to reliably estimate their frequency or establish a causal relationship to drug exposure.

- Thyroid conditions: hyperthyroidism, thyroiditis, thyrotoxicosis, and hypothyroidism.

8 USE IN SPECIFIC POPULATIONS

8.1 Pregnancy

Risk Summary

Based on its mechanism of action, LYMPHIR can cause fetal harm when administered to a pregnant woman [see Clinical Pharmacology (12.1)]. There are no available data on the use of LYMPHIR in pregnant women to evaluate for a drug-associated risk. No animal reproductive and developmental toxicity studies have been conducted with denileukin diftitox.

Denileukin diftitox-cxdl causes depletion of regulatory T lymphocytes (Treg), immune activation, and capillary leak syndrome, compromising pregnancy maintenance. Advise pregnant women of the potential risk to a fetus.

In the U.S. general population, the estimated background risk of major birth defects and miscarriage in clinically recognized pregnancies are 2-4% and 15-20%, respectively.

8.2 Lactation

Risk Summary

No data are available regarding the presence of denileukin diftitox-cxdl in human milk, the effects on the breastfed child, or on milk production. Because of the potential for serious adverse reactions in breastfed children, advise women not to breastfeed during treatment with LYMPHIR and for 7 days after the last dose.

8.3 Females and Males of Reproductive Potential

Based on its mechanism of action, LYMPHIR can cause fetal harm when administered to a pregnant woman [see Use in Specific Populations (8.1)] .

Pregnancy Testing

Verify the pregnancy status of females of reproductive potential prior to initiating LYMPHIR [see Use in Specific Populations (8.1)] .

Contraception

Females

Advise females of reproductive potential to use effective contraception during treatment with LYMPHIR and for 7 days after the last dose.

Infertility

Males

Based on findings in rats, male fertility may be compromised by treatment with LYMPHIR [see Nonclinical Toxicology (13.1)] . The reversibility of the effect on fertility is unknown.

8.4 Pediatric Use

Safety and effectiveness of LYMPHIR in pediatric patients have not been established.

8.5 Geriatric Use

Of the 69 patients with Stage I-III relapsed or refractory CTCL who received LYMPHIR, 34 patients (49%) were 65 years of age and older and 10 patients (14%) were 75 years of age and older [see Clinical Studies (14)] . Clinical studies of LYMPHIR did not include sufficient numbers of patients 65 years of age and older to determine whether they respond differently from younger adult patients.

11 DESCRIPTION

Denileukin diftitox-cxdl, an IL2-receptor-directed cytotoxin, is a recombinant DNA-derived fusion protein composed of the amino acid sequences for diphtheria toxin fragments A and B (Met1-Thr387)-His and the sequence for human interleukin-2 (IL-2; Ala1-Thr133). It is produced in an E. coliexpression system and has a molecular weight of 58 kD. Neomycin is used in the fermentation process but is undetectable in the final product.

LYMPHIR (denileukin diftitox-cxdl) for injection is supplied as a sterile, white, lyophilized cake in a single-dose vial for intravenous use after reconstitution and dilution. Each vial of LYMPHIR contains 300 mcg of denileukin diftitox-cxdl, citric acid monohydrate (4.2 mg), edetate disodium (0.04 mg), methionine (3 mg), polysorbate 20 (1.2 mg), and trehalose (100.4 mg). Sodium hydroxide is used to adjust the pH of the formulation buffer. Following reconstitution with 2.1 mL of Sterile Water for Injection, USP, the resulting concentration of denileukin diftitox-cxdl is 150 mcg/mL at pH approximately 7.

12 CLINICAL PHARMACOLOGY

12.1 Mechanism of Action

Denileukin diftitox-cxdl is a fusion protein designed to direct the cytocidal action of diphtheria toxin (DT) to cells which express the IL-2 receptor. After uptake into the cell, the DT fragment is cleaved and the free DT fragments inhibit protein synthesis, resulting in cell death. Denileukin diftitox-cxdl demonstrated the ability to deplete immunosuppressive regulatory T lymphocytes (Tregs) and antitumor activity through a direct cytocidal action on IL-2R-expressing tumors.

12.2 Pharmacodynamics

Higher denileukin diftitox-cxdl exposures were associated with higher incidence of capillary leak syndrome, hepatotoxicity, treatment discontinuations due to adverse reactions, and adverse reactions Grade ≥3 following administration of LYMPHIR. Denileukin diftitox-cxdl time course of pharmacodynamic response is unknown.

12.3 Pharmacokinetics

Following a single dose of denileukin diftitox-cxdl 9 mcg/kg via 1-hr infusion on Cycle 1, Day 1 in patients with CTCL, the geometric mean (coefficient of variation [CV]%) maximum serum concentration (Cmax) was 94.4 ng/mL (77%) and area under the concentration over time curve (AUC0-inf) was 20700 ng· min/L (60%). There is no accumulation after repeated daily dosing.

Distribution

The geometric mean (CV%) volume of distribution of denileukin diftitox-cxdl is 5.0 L (43%) on Cycle 1, Day 1.

Elimination

The geometric mean (CV%) clearance is 36.5 mL/min (73%) after the first dose of denileukin diftitox-cxdl at the recommended dose level. The arithmetic mean (CV%) denileukin diftitox-cxdl terminal half-life is 112 minutes (31%) on Cycle 1, Day 1.

Metabolism

Denileukin diftitox-cxdl is expected to be metabolized into small peptides by catabolic pathways.

Specific Populations

No clinically significant differences in the pharmacokinetics of LYMPHIR were observed based on age (23 to 86 years), body weight (39 kg to 148 kg), sex, race (White, African American/Black, Asian), ECOG status (0 to 2), mild to moderate renal impairment (estimated creatinine clearance [CLcr] by Cockcroft–Gault equation: 30 to 89 mL/min), or mild hepatic impairment (total bilirubin less than or equal to upper limit of normal [ULN] and AST greater than ULN, or total bilirubin 1 to 1.5 times ULN and any AST). The effect of moderate or severe hepatic impairment (total bilirubin greater than 1.5 times ULN with any AST) and severe renal impairment (CLcr 15 to 29 mL/min) on denileukin diftitox-cxdl pharmacokinetics is unknown.

12.6 Immunogenicity

The observed incidence of anti-drug antibodies (ADAs) is highly dependent on the sensitivity and specificity of the methods. Differences in ADA assay methods may preclude meaningful comparisons of the incidence of ADAs in the studies of denileukin diftitox-cxdl.

In Study 302, among patients with any stage CTCL who received LYMPHIR 9 mcg/kg/day (median duration of treatment: 6 cycles),

- Of the 90 subjects with immunogenicity results at baseline, 74% (67/90) of subjects had pre-existing antibodies to denileukin diftitox-cxdl and 7.8% (7/90) of the subjects had neutralizing anti-denileukin diftitox-cxdl antibodies. The high prevalence of ADA at baseline was anticipated due to vaccination against diphtheria toxin. Among these subjects, 5.6% (5/90) of the subjects had ADAs against IL-2 but none had neutralizing antibodies against IL-2.
- Of the 84 subjects evaluable for treatment-emergent (TE) ADA across all cycles after treatment with LYMPHIR, 88% (74/84) and 82% (69/84) of subjects developed treatment-emergent ADAs against denileukin diftitox-cxdl and IL-2, respectively. Among these subjects, 80% (67/84) developed neutralizing antibodies against denileukin diftitox-cxdl and 13% (11/84) developed neutralizing antibodies against the IL-2 domain of denileukin diftitox-cxdl.
- Treatment with LYMPHIR leads to an increase in anti-denileukin diftitox-cxdl and anti-IL-2 antibody titers. In subjects with treatment-emergent ADA during Study 302, the median anti-denileukin diftitox-cxdl antibody titers were 182, 260, 153, and 94 times higher than baseline at C2D1, C3D1, C5D1, and C8D1 and the anti-IL2 antibody titers were 2, 49, 437, and 1312 times higher than baseline at these same visits.

Anti-Drug Antibody Effects on Pharmacokinetics

The presence of ADA is associated with a reduction in the measured serum concentration. In a subset of patients with treatment-emergent anti-denileukin diftitox-cxdl and/or anti-IL-2 antibodies during Study 302, the geometric mean ratio for denileukin diftitox-cxdl Cmaxand AUC(0-t)is 37% and 19% in Cycle 3 compared to Cycle 1, and is 30% and 15% in Cycle 5 compared to Cycle 1. The decrease in denileukin diftitox-cxdl concentration does not appear to adversely impact safety and efficacy.

13 NONCLINICAL TOXICOLOGY

13.1 Carcinogenesis, Mutagenesis, Impairment of Fertility

There have been no studies to assess the carcinogenic potential of denileukin diftitox-cxdl. Denileukin diftitox-cxdl showed no evidence of mutagenicity in the Ames test and the chromosomal aberration assay. There have been no studies to assess the effect of denileukin diftitox on fertility. In a 14-week repeat-dose toxicology study in rats, denileukin diftitox-cxdl caused toxicity to male reproductive organs including atrophy of the epididymis, prostate gland, and testes and single cell necrosis in the epididymis.

14 CLINICAL STUDIES

Relapsed or Refractory CTCL

The efficacy of LYMPHIR was evaluated in Study 302 (NCT01871727), an open-label, single-arm, multicenter trial in patients with relapsed or refractory Stage I to IV CTCL. Eligible patients were required to have expression of CD25 on ≥ 20% of biopsied malignant cells by immunohistochemistry .The study excluded patients with significant cardiac disease or uncontrolled infections. Patients received LYMPHIR at 9 mcg/kg as an intravenous infusion daily from Day 1 through Day 5 of each 21-day cycle. Patients continued to receive LYMPHIR until disease progression or unacceptable toxicity.

The efficacy population includes 69 patients with relapsed or refractory Stage I to III CTCL. Of the 69 patients, the median age was 64 years (range: 28 to 87 years), 65% were male, 73% were White, 19% Black or African American, 1% Asian, and 14% Hispanic or Latino. The CTCL disease stage was IA in 7%, IB in 23%, IIA in 13%, IIB in 35%, IIIA in 12%, and IIIB in 10%. The median number of prior therapies was 4 (range: 1 to 18), including both skin-directed and systemic therapies. Prior therapies included photodynamic therapy (56%), total skin electron beam therapy (42%), systemic retinoids (49%), methotrexate/pralatrexate (49%), histone deacetylase inhibitor (35%), brentuximab vedotin (26%) and mogamulizumab (12%).

Efficacy was established based on objective response rate (ORR), according to ISCL/EORTC Global Response Score (GRS) per Independent Review Committee (Olsen 2011). Efficacy results are shown in Table 5.

Table 5: Efficacy Results of Study 302
Efficacy Endpoint | LYMPHIR; 9 mcg/kg/day (N=69)
ORR (GRS)%a (95% CIb) | 36% (25, 49)
Complete Response | 9%
Partial Response | 27%
Duration of Responsec; Range, months; Duration ≥ 6 months, n (%); Duration ≥ 12 months, n (%) | 3.0+, 23.5+; 13 (52%); 5 (20%)

aORR, objective response rate per Olsen, et al (2011) Global Response Score (GRS), by Independent Review Committee (IRC).
bCI, confidence interval
cThe median (95% CI) DOR using Kaplan-Meier (KM) estimate was not estimable (NE) among the 25 subjects due to censoring.

Median time to response was 1.4 months (range: 0.7 to 5.6 months).

Among responders, the median follow-up for duration of response was 6.5 months (range: 3.5+, 23.5+ months).

16 HOW SUPPLIED/STORAGE AND HANDLING

How Supplied

LYMPHIR (denileukin diftitox-cxdl) for injection is supplied as a sterile, white, lyophilized cake for reconstitution in a single-dose vial containing 300 mcg denileukin diftitox-cxdl. Each carton contains one vial:

NDC 52658-7777-1

Storage and Handling

Store LYMPHIR in a refrigerator between 2°C to 8°C (36°F to 46°F) in the original carton to protect from light. Do not freeze.

17 PATIENT COUNSELING INFORMATION

Discuss the following with patients prior to and during treatment with LYMPHIR.

Capillary Leak Syndrome

Inform patients of the signs and symptoms of capillary leak syndrome. Advise patients to contact their healthcare provider immediately if any signs or symptoms of capillary leak syndrome occur, including edema or change in blood pressure. Instruct patients to weigh themselves daily and report weight gain [see Warnings and Precautions (5.1)] .

Visual Impairment

Inform patients that if they experience symptoms of visual impairment, such as changes in visual acuity, changes in color vision, or blurred vision, they should report it promptly [see Warnings and Precautions (5.2)] .

Infusion-Related Reactions

Inform patients of the signs and symptoms of infusion-related reactions. Advise patients to contact their healthcare provider immediately if any signs or symptoms of infusion-related reaction occur, including fever, chills, breathing problems, chest pain, or hives [see Warnings and Precautions (5.3)] .

Hepatotoxicity

Advise patients that liver enzyme elevations can occur and that they should report symptoms that may indicate liver toxicity, including fatigue, anorexia, right upper abdominal discomfort, dark urine, or jaundice [see Warnings and Precautions (5.4)].

Embryo-Fetal Toxicity

Advise pregnant women and female patients of reproductive potential of the potential risk to a fetus. Advise female patients of reproductive potential to inform their healthcare provider of a known or suspected pregnancy and to use effective contraception for 7 days after the last dose [see Warnings and Precautions (5.5), Use in Specific Populations (8.1, 8.3)] .

Lactation

Advise women not to breastfeed during treatment with LYMPHIR and for 7 days after the last dose [see Use in Specific Populations (8.2)] .

Manufactured by:
Citius Oncology, Inc.
Cranford, NJ 07016
US License No. 2290

LYMPHIR™ is the trademark of Citius Oncology, Inc.

© 2024 Citius Oncology, Inc.

PRINCIPAL DISPLAY PANEL

NDC 52658-7777-1

LYMPHIR™
(denileukin diftitox-cxdl)
For Injection
300 mcg/vial

For Intravenous Infusion
After Reconstitution and Dilution.
Single-dose Vial.
Discard unused portion.

1 Vial Rx Only